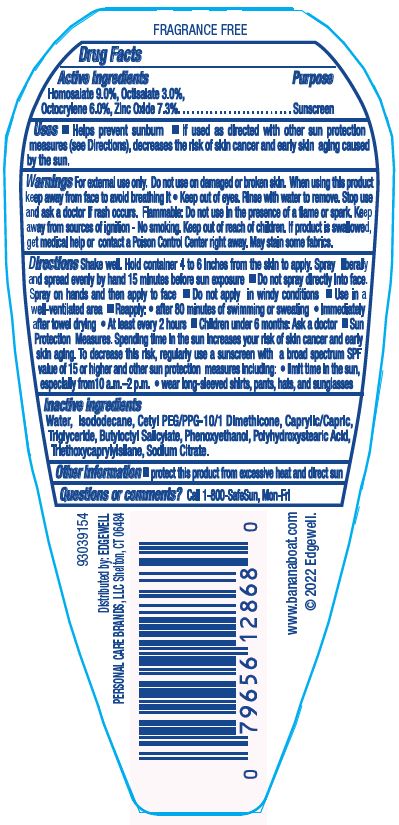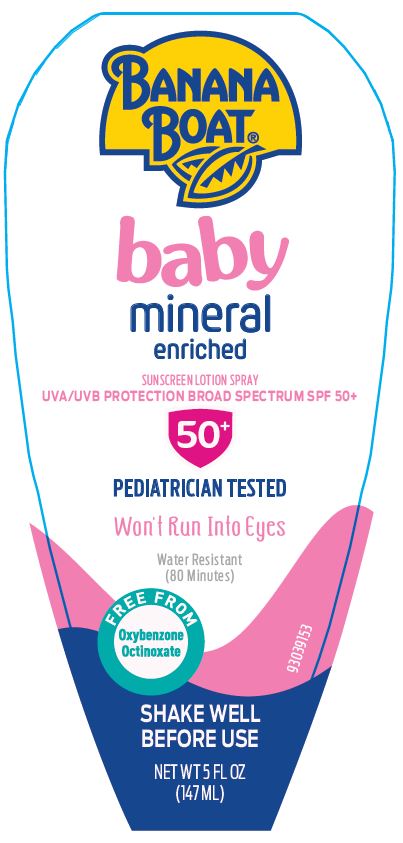 DRUG LABEL: Banana Boat Baby Mineral Enriched Sunscreen UVA/UVB Protection Broad Spectrum SPF 50PLUS
NDC: 63354-682 | Form: LOTION
Manufacturer: Edgewell Personal Care Brands LLC
Category: otc | Type: HUMAN OTC DRUG LABEL
Date: 20251117

ACTIVE INGREDIENTS: OCTOCRYLENE 6 g/100 g; OCTISALATE 3 g/100 g; HOMOSALATE 9 g/100 g; ZINC OXIDE 7.3 g/100 g
INACTIVE INGREDIENTS: CETYL PEG/PPG-10/1 DIMETHICONE (HLB 2); TRIETHOXYCAPRYLYLSILANE; SODIUM CITRATE; WATER; PHENOXYETHANOL; BUTYLOCTYL SALICYLATE; MEDIUM-CHAIN TRIGLYCERIDES; POLYHYDROXYSTEARIC ACID (2300 MW); ISODODECANE

Active Ingredients

Homosalate 9.0%, Octisalate 3.0%, Octocrylene 6.0%, Zinc Oxide 7.3%.

Purpose

Sunscreen

Uses

• Helps prevent sunburn • if used as directed with other sun protection measures (see Directions), decreases the risk of skin cancer and early skin aging caused by the sun.

Warnings

For external use only.

Flammable: Do not use in the presence of a flame or spark. Keep away from sources of ignition - No smoking.

May stain some fabrics.

Do not use

on damaged or broken skin

When using this product

keep away from face to avoid breathing it • Keep out of eyes. Rinse with water to remove.

Stop use

and ask a doctor if rash occurs.

Keep out of reach of children.

If product is swallowed, get medical help or contact a Poison Control Center right away.

Directions

Shake well. Hold container 4 to 6 inches from the skin to apply. Spray liberally and spread evenly by hand 15 minutes before sun exposure • Do not spray directly into face. Spray on hands and then apply to face • Do not apply in windy conditions • Use in a well-ventilated area • Reapply: • after 80 minutes of swimming or sweating • Immediately after towel drying • At least every 2 hours • Children under 6 months: Ask a doctor

Sun Protection Measures. Spending time in the sun increases your risk of skin cancer and early skin aging. To decrease this risk, regularly use a sunscreen with a broad spectrum SPF value of 15 or higher and other sun protection measures including: • limit time in the sun, especially from 10 a.m.–2 p.m. • wear long-sleeved shirts, pants, hats, and sunglasses

Inactive ingredients

Water, Isododecane, Cetyl PEG/PPG-10/1 Dimethicone, Caprylic/Capric, Triglyceride, Butyloctyl Salicylate, Phenoxyethanol, Polyhydroxystearic Acid, Triethoxycaprylylsilane, Sodium Citrate.

Other Information

• protect this product from excessive heat and direct sun

Questions or comments?

Call 1-800-SafeSun, Mon-Fri

Principal Display Panel

BANANA BOAT®
baby
mineral
enriched
SUNSCREEN LOTION SPRAY
UVA/UVB PROTECTION BROAD SPECTRUM SPF 50+
50+
PEDIATRICIAN TESTED
Won't Run Into Eyes
Water Resistant
(80 Minutes)
FREE FROM
Oxybenzone
Octinoxate
SHAKE WELL
BEFORE USE
NET WT 5 FL OZ
(147mL)